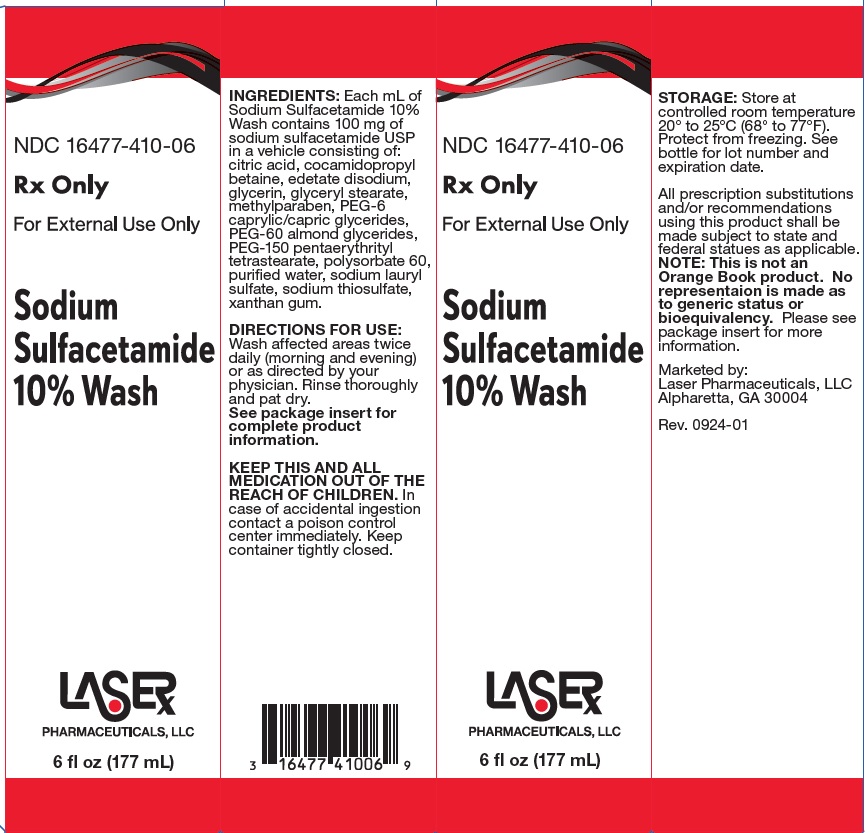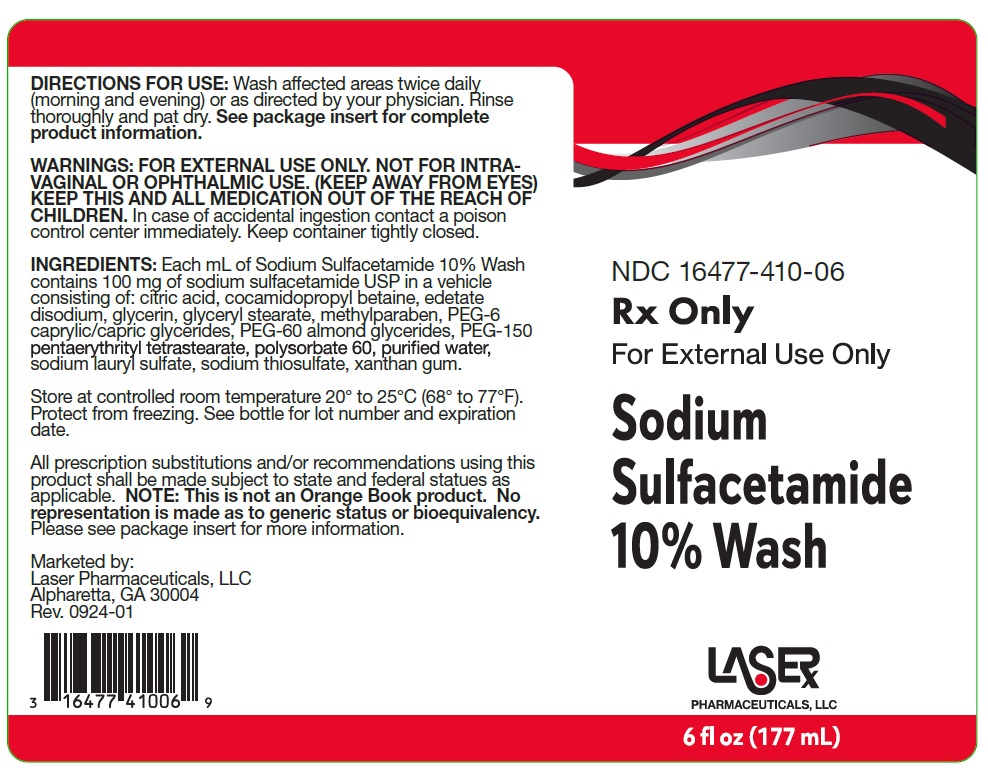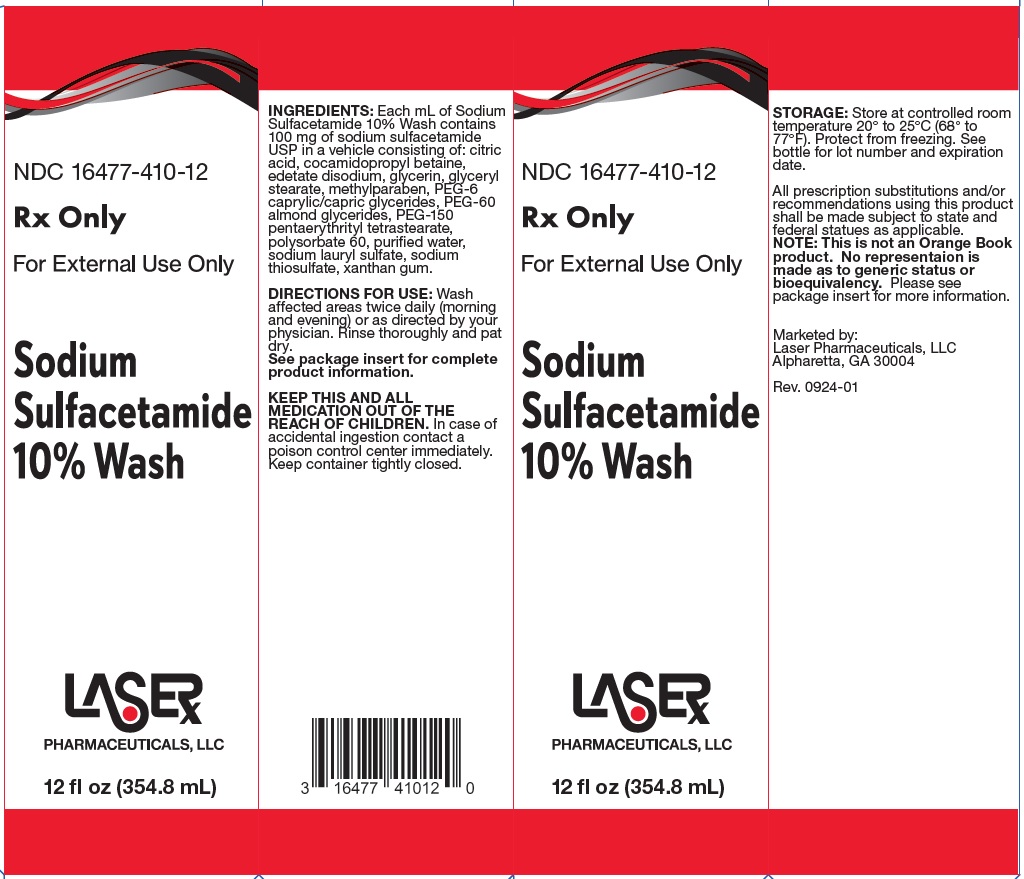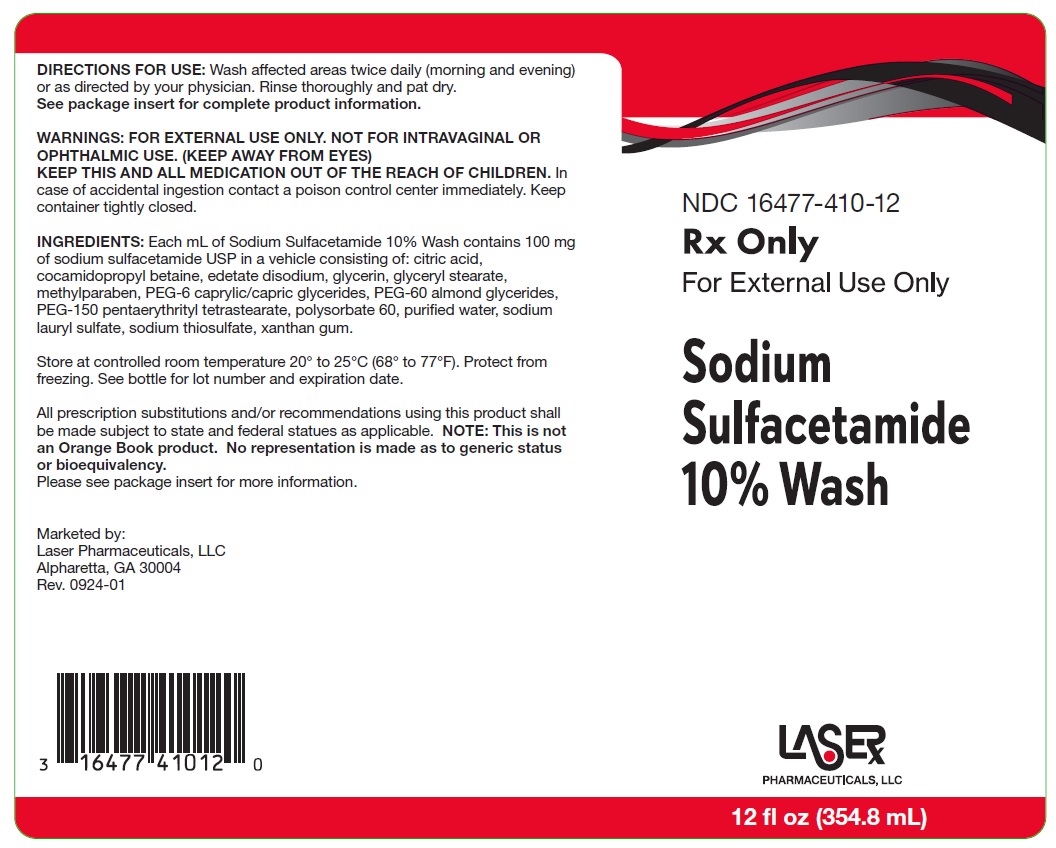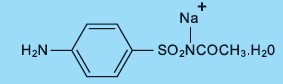 DRUG LABEL: Sodium Sulfacetamide
NDC: 16477-410 | Form: LIQUID
Manufacturer: Laser Pharmaceuticals, LLC
Category: prescription | Type: HUMAN PRESCRIPTION DRUG LABEL
Date: 20250423

ACTIVE INGREDIENTS: SULFACETAMIDE SODIUM 100 mg/1 mL
INACTIVE INGREDIENTS: XANTHAN GUM; METHYLPARABEN; GLYCERYL STEARATE SE; COCAMIDOPROPYL BETAINE; GLYCERIN; PEG-6 CAPRYLIC/CAPRIC GLYCERIDES; PEG-60 ALMOND GLYCERIDES; PEG-150 PENTAERYTHRITYL TETRASTEARATE; WATER; EDETATE DISODIUM ANHYDROUS; POLYSORBATE 60; SODIUM THIOSULFATE; SODIUM LAURYL SULFATE; CITRIC ACID MONOHYDRATE

Sodium Sulfacetamide 10% Wash

Description:

Each mL contains 100 mg of sodium sulfacetamide in a vehicle consisting of: citric acid, cocamidopropyl betaine, edetate disodium, glycerin, glyceryl stearate, methylparaben, PEG-6 caprylic/capric glycerides, PEG-60 almond glycerides, PEG-150 pentaerythrityl tetrastearate, polysorbate 60, purified water, sodium lauryl sulfate, sodium thiosulfate, xanthan gum. Sodium sulfacetamide is a sulfonamide with antibacterial activity. Sodium sulfacetamide is C 8H 9N 2NaO 3S•H2O with molecular weight of 254.24. Chemically, sodium sulfacetamide is N-[(4-aminophenyl) sulfonyl]-acetamide, monosodium salt, monohydrate. The structural formula is:

Sodium sulfacetamide is an odorless, white, crystalline powder with a bitter taste. It is freely soluble in water, sparingly soluble in alcohol, while practically insoluble in benzene, in chloroform and in ether.

CLINICAL PHARMACOLOGY:

Sodium sulfacetamide exerts a bacteriostatic effect against sulfonamide sensitive Gram-positive and Gram-negative microorganisms commonly isolated from secondary cutaneous pyogenic infections. It acts by restricting the synthesis of folic acid required by bacteria for growth, by its competition with para-aminobenzoic acid. There is no clinical data available on the degree and rate of systemic absorption of Sodium Sulfacetamide 10% Wash when applied to the skin or scalp. However, significant absorption of sodium sulfacetamide through the skin has been reported. The following in vitro data is available but the clinical significance is unknown. Organisms that show susceptibility to sodium sulfacetamide are: Streptococci, Staphylococci, E. coli, Klebsiella pneumoniae,Pseudomonas pyocyanea, Salmonella species, Proteus vulgaris, Nocardia and Actinomyces.

INDICATIONS AND USAGE:

Sodium Sulfacetamide 10% Wash is intended for topical application in the following scaling dermatoses: seborrheic dermatitis and seborrhea sicca (dandruff). It also is indicated for the treatment of secondary bacterial infections of the skin due to organisms susceptible to sulfonamides.

CONTRAINDICATIONS:

Sodium Sulfacetamide 10% Wash is contraindicated in persons with known or suspected hypersensitivity to sulfonamides or to any of the ingredients of the product.

WARNINGS:

Sulfonamides are known to cause Stevens-Johnson syndrome in hypersensitive individuals. Stevens-Johnson syndrome also has been reported following the use of sodium sulfacetamide topically. Cases of drug-induced systemic lupus erythematosus from topical sulfacetamide also have been reported. In one of these cases, there was a fatal outcome. KEEP THIS AND ALL
MEDICATION OUT OF THE REACH OF CHILDREN.

PRECAUTIONS:

For external use only. Not for ophthalmic use. General: Nonsusceptible organisms, including fungi, may proliferate with the use of this preparation.
Hypersensitivity reactions may recur when a sulfonamide is readministered, irrespective of the route of administration, and cross hypersensitivity between different sulfonamides may occur. If Sodium Sulfacetamide 10% Wash produces signs of hyper sensitivity or other untoward reactions, discontinue use of the preparation. Systemic absorption of topical sulfonamides is greater following application to large, infected, abraded, denuded or severely burned areas. Under these circumstances, any of the adverse effects produced by the systemic administration of these agents could potentially occur, and appropriate observations and laboratory determinations should be performed.

Information For Patients:

Patients should discontinue the use of Sodium Sulfacetamide 10% Wash if the condition becomes worse or if a rash develops in the area being treated or elsewhere. The use of Sodium Sulfacetamide 10% Wash also should be discontinued promptly and the physician notified if any arthritis, fever or sores in the mouth develop.

Drug Interactions:

Sodium Sulfacetamide 10% Wash is incompatible with silver preparations.

Pharmacology:

Sodium Sulfacetamide 10% Wash has a bacteriostatic effect against Gram-positive and Gram-negative miroorganisms commonly isolated from secondary cutaneous pyogenic infections.

Carcinogenesis, Mutagenesis and Impairment of Fertility:

Long-term animal studies for carcinogenic potential have not been performed on Sodium Sulfacetamide 10% Wash to date. Studies on reprodution and fertility also have not been performed. Chromosomal nondisjunction in the yeast, Saccharomyces cerevisiae, following application of sodium sulfacetamide has been reported. The significance of this finding to the topical use of sodium sulfacetamide in the human is unknown.

Pregnancy: Category C:

Animal reproduction studies have not been conducted with Sodium Sulfacetamide 10% Wash. It is also not known whether Sodium Sulfacetamide 10% Wash can affect reproduction capacity or cause fetal harm when administered to a pregnant woman. This Sodium Sulfacetamide 10% Wash should be used by a pregnant woman only if clearly needed or when potential benefits outweigh potential hazards to the fetus.

Nursing Mothers:

It is not known whether this drug is excreted in human milk. Because many drugs are excreted in human milk, caution should be exercised when this product is administered to a nursing woman.

Pediatric Use:

Safety and effectiveness in chlidren under the age of 12 years have not ben established.

ADVERSE REACTIONS

Reports of irritation and hypersensitivity to sodium sulfacetamide are uncommon. The following adverse reactions, reported after administration of sterile ophthalmic sodium sulfacetamide, are noteworthy: instances of Stevens-Johnson syndrome and instances of local hypersensitivity which progressed to a syndrome resembling systemic lupus erythematosus; in one case a fatal outcome was reported (see WARNINGS).

OVERDOSAGE:

The oral LD50 of sulfacetamide in mice is 16.5 g/kg. In the event of overdosage, emergency treatment should be started immediately.

Manifestations: Overdosage may cause nausea and vomiting. Large oral overdosage may cause hematuria, crystalluria and renal shutdown due to the precipitation of sulfa crystals in the renal tubules and the urinary tract. For treatment, contact your local Poison Control Center or your doctor.

DOSAGE AND ADMINISTRATION:

Seborrheic dermatits including seborrhea sica - Sodium Sulfacetamide 10% Wash: Wash affected areas twice daily (morning and evening), or as directed by your phyiscian. Avoid contact with eyes or mucous membranes. Wet skin and liberally apply to areas to be cleansed, message gently into skin working into a full lather, rinse thoroughly/pat dry and repeat after 10 to 20 seconds. Rinsing with plain water will remove any excess medication. Repeat application as described for eight to ten days. If skin dryness occurs it may be controlled by rinsing cleanser off sooner or using less frequently. Regular shampooing following Sodium Sulfacetamide 10% Wash is not necessary but the hair should be shampooed at least once a week. As the condition subsides, the interval between applications may be lengthened. Applications once or twice a week may prevent recurrence. Should the condition recur after stopping therapy, the application of Sodium Sulfacetamide 10% Wash should be reinitiated as at the beginning of treatment. Secondary Cutaneous Bacterial Infections - Wet skin and liberally apply to areas to be cleansed, massage gently into skin for 10-20 seconds working into a full lather, rinse thoroughly and pat dry. Rinsing with plain water will remove any excess medication. Repeat application as described for eight to ten days. If skin dryness occurs it may be controlled by rinsing cleanser off sooner or using less often.

HOW SUPPLIED:

Sodium Sulfacetamide 10% Wash is supplied in the following size(s): 6 fl. oz. (177 mL) bottle, NDC 16477-410-06, and 12 fl. oz (354.8mL) bottle, NDC 16477-410-12

STORAGE:

Store at 20°C to 25°C (68°F to 77°F), excursions permitted between 15°C and 30°C (between 59°F and 86°F). See USP Controlled Room Temperature. Protect from freezing.

NOTICE: Store upright. Protect from freezing and excessive heat. The wash may tend to darken slightly on storage. Slight discoloration does not impair the efficacy or safety of the product. Occasionally, a slight discoloration of fabric may occur when an excessive amount of the product is used and comes in contact with white fabrics. This discoloration, however, presents no problem, as it is readily removed by ordinary laundering without bleaches.

All prescription substitutions and/or recommendations using this product shall be made subject to state and federal statutes as applicable. Please NOTE: This is not an Orange Book product and has not been subjected to FDA therapeutic equivalency or other equivalency testing. No representation is made as to generic status or bioequivalency. Each person recommending a prescription substitution using this product shall make such recommendations based on each such person’s professional opinion and knowledge, upon evaluating the active ingredients, inactive ingredients (excipients) and other chemical information provided herein. To report a serious adverse event or obtain product information, call 1-844-302-5227.

PACKAGE LABEL

NDC 16477-410-06

Rx Only

For External Use Only

Sodium

Sulfacetamide

10% Wash

LASER Pharmaceuticals, LLC

6 fl oz (177 mL)

INGREDIENTS: Each mL of Sodium Sulfacetamide 10% Wash contains 100 mg of sodium sulfacetaide USP in a vehicle consisting of: citric acid, cocamidopropyl betaine, edetate disodium, glycerin, glyceryl stearate, methylparaben, PEG-6 caprylic/capric glycerides, PEG-60 almond glycerides, PEG-150 pentaerythrityl tetrastearate, polysorbate 60, purified water, sodium lauryl sulfate, sodium thiosulfate, xanthan gum.

DIRECTIONS FOR USE:

Wash affected areas twice daily (morning and evening) or as directed by your physician. Rinse thoroughly and pat dry.

See package insert for complete product information.

KEEP THIS AND ALL MEDICATION OUT OF THE REACH OF CHILDREN. In case of accidential ingestion contact a poison control center immediatly. Keep container tightly closed.

STORAGE: Store at controlled room temperature 20 to 25C (68 to 77F). Protect from freezing. See bottle for lot number and expiration date.

All prescription substitutions and/or recommendations using this produt shall be made subject to state and federal statutes as applicable.

NOTE: This is not an Orange Book product. No representation is made as to generic status or bioequivalency. Please see pakage insert for more informatio.

Marketed by:

Laser Pharmaceuticals, LLC

Alpharetta, GA 30004

Rev. 0924-01